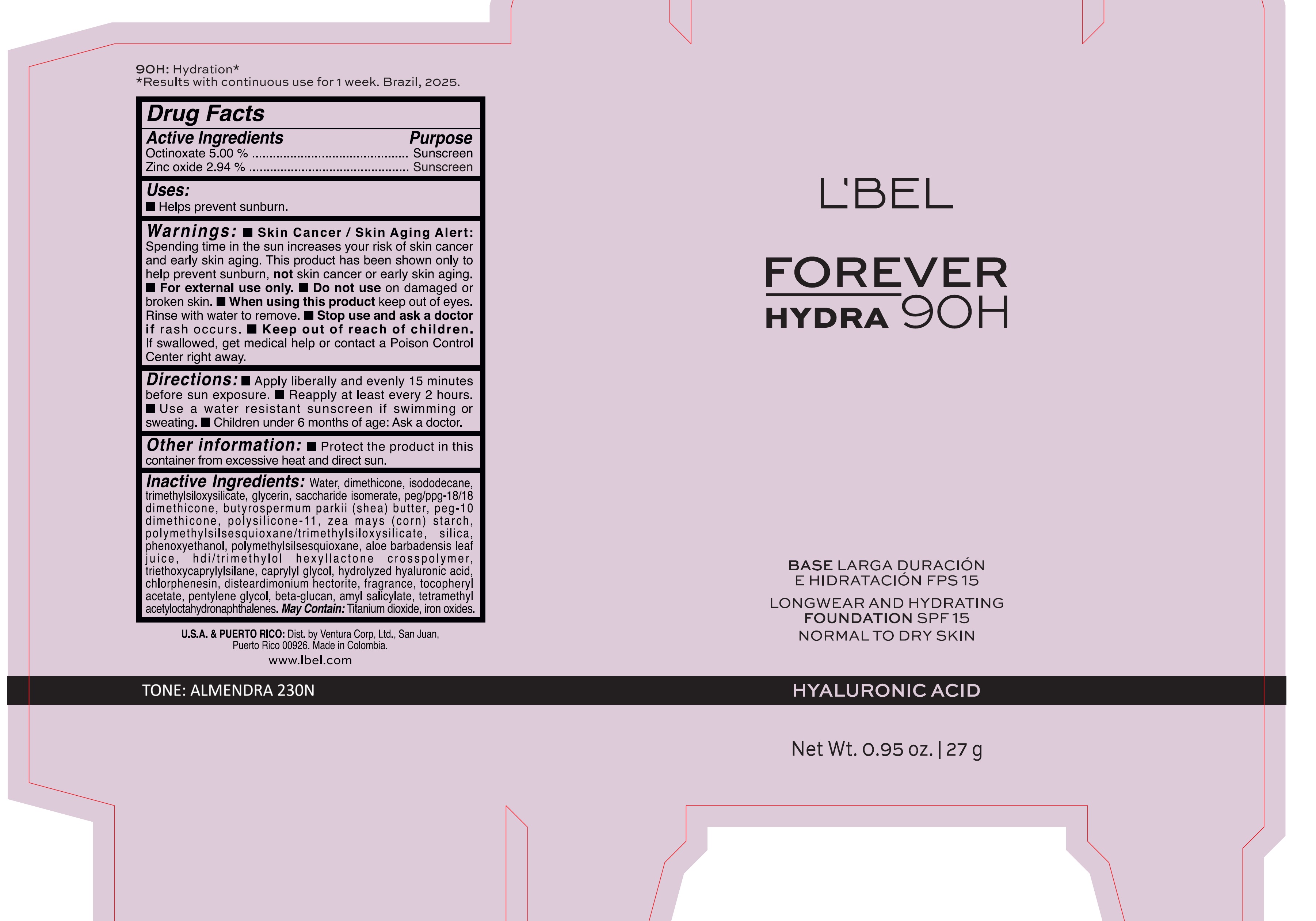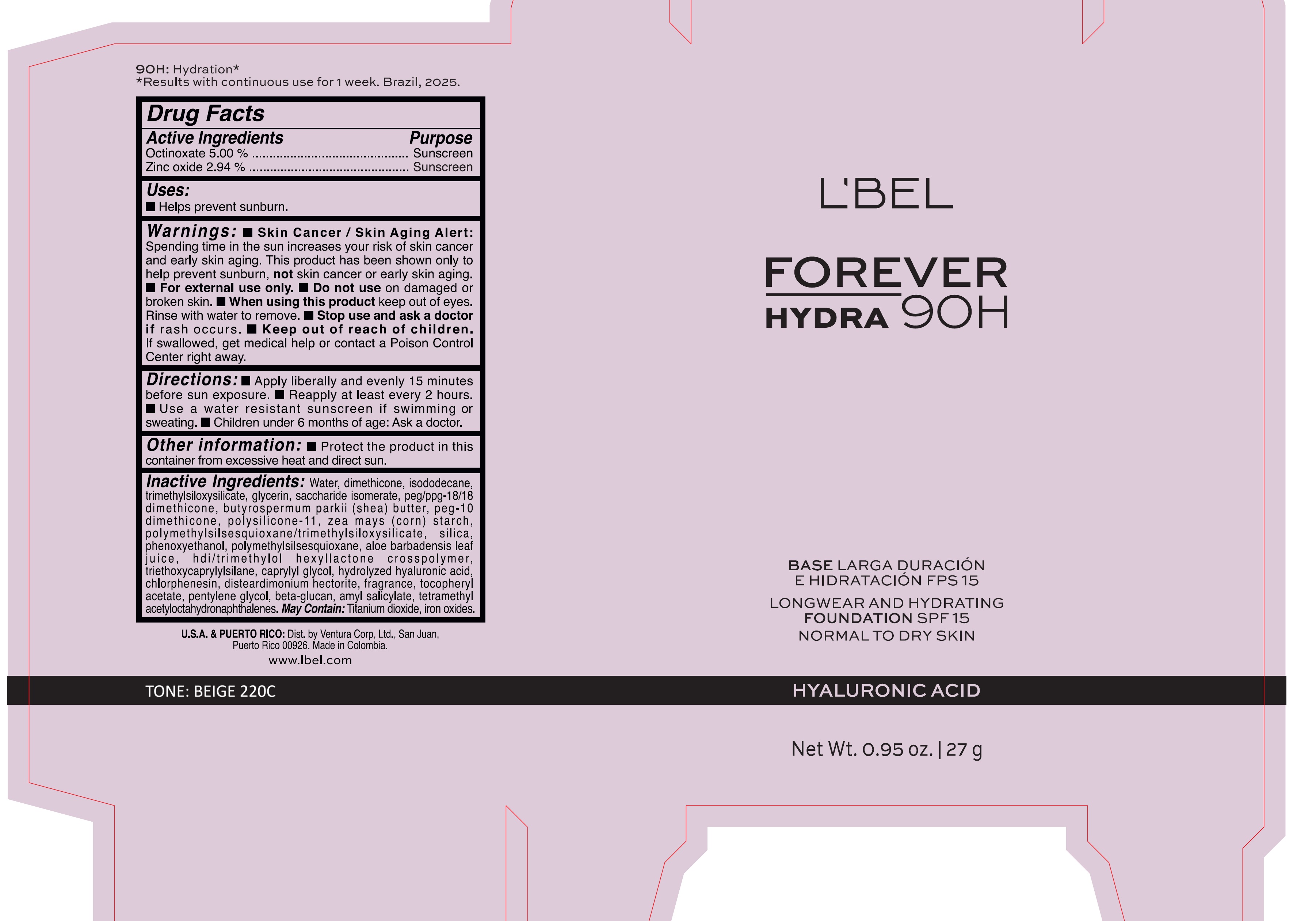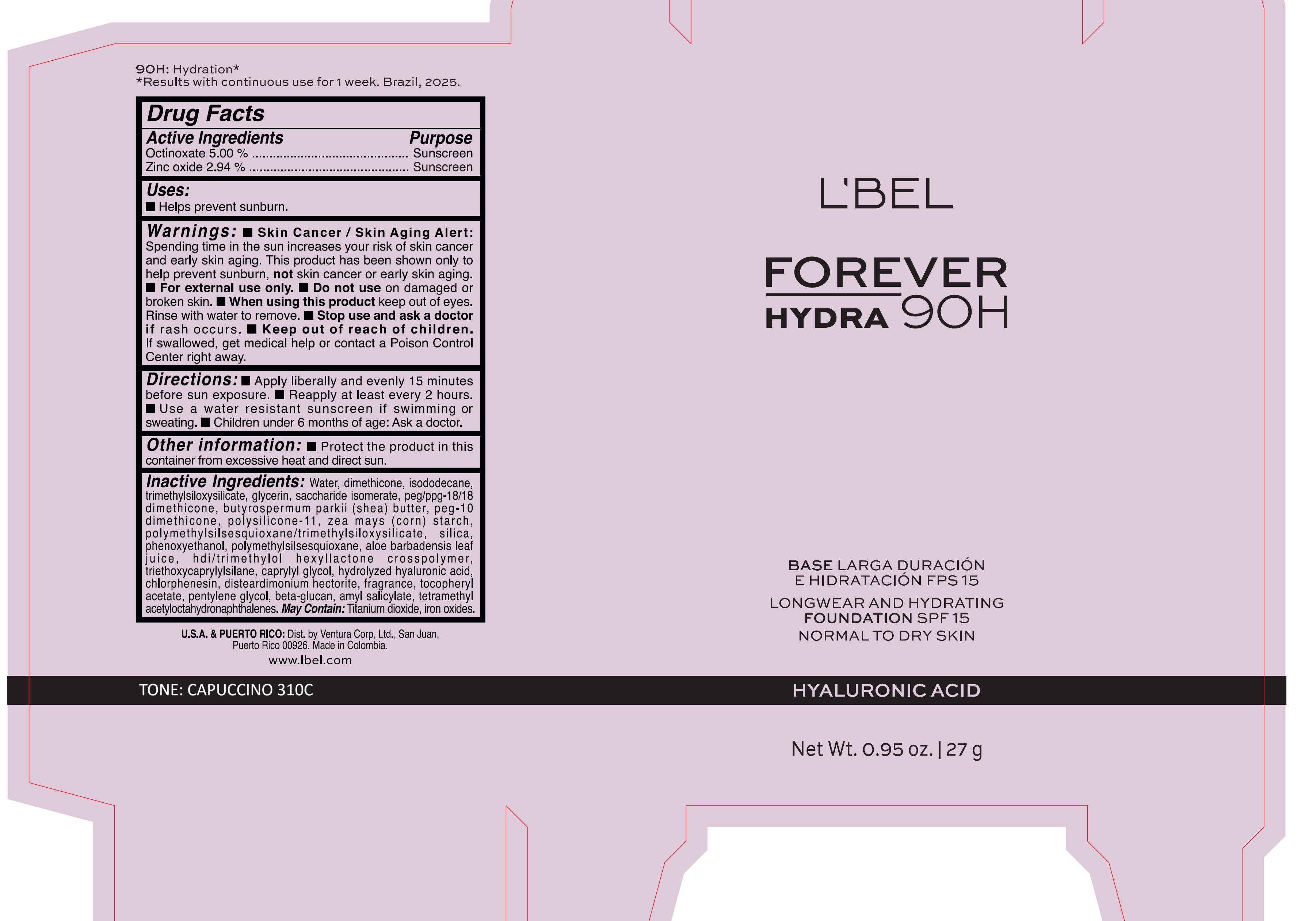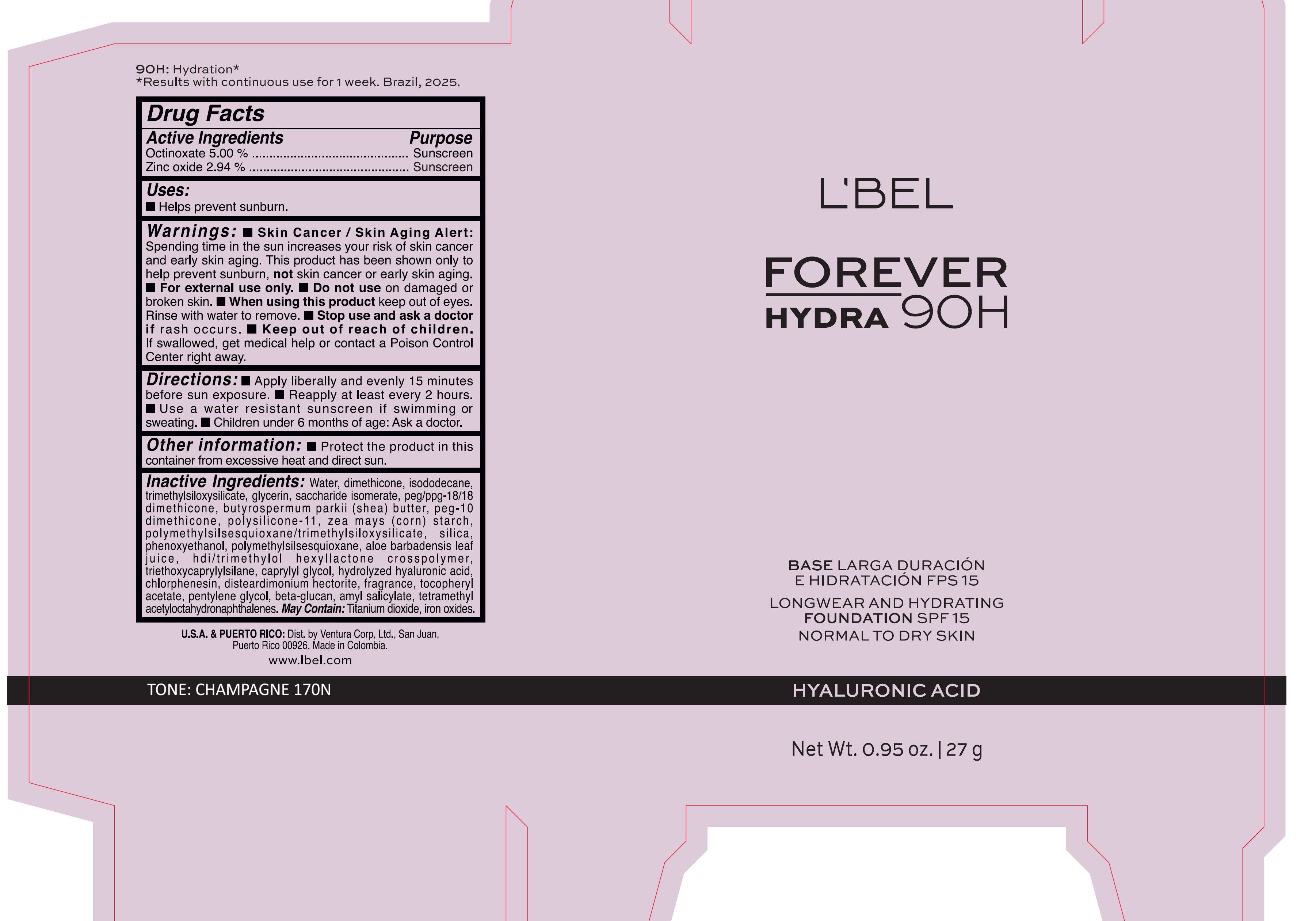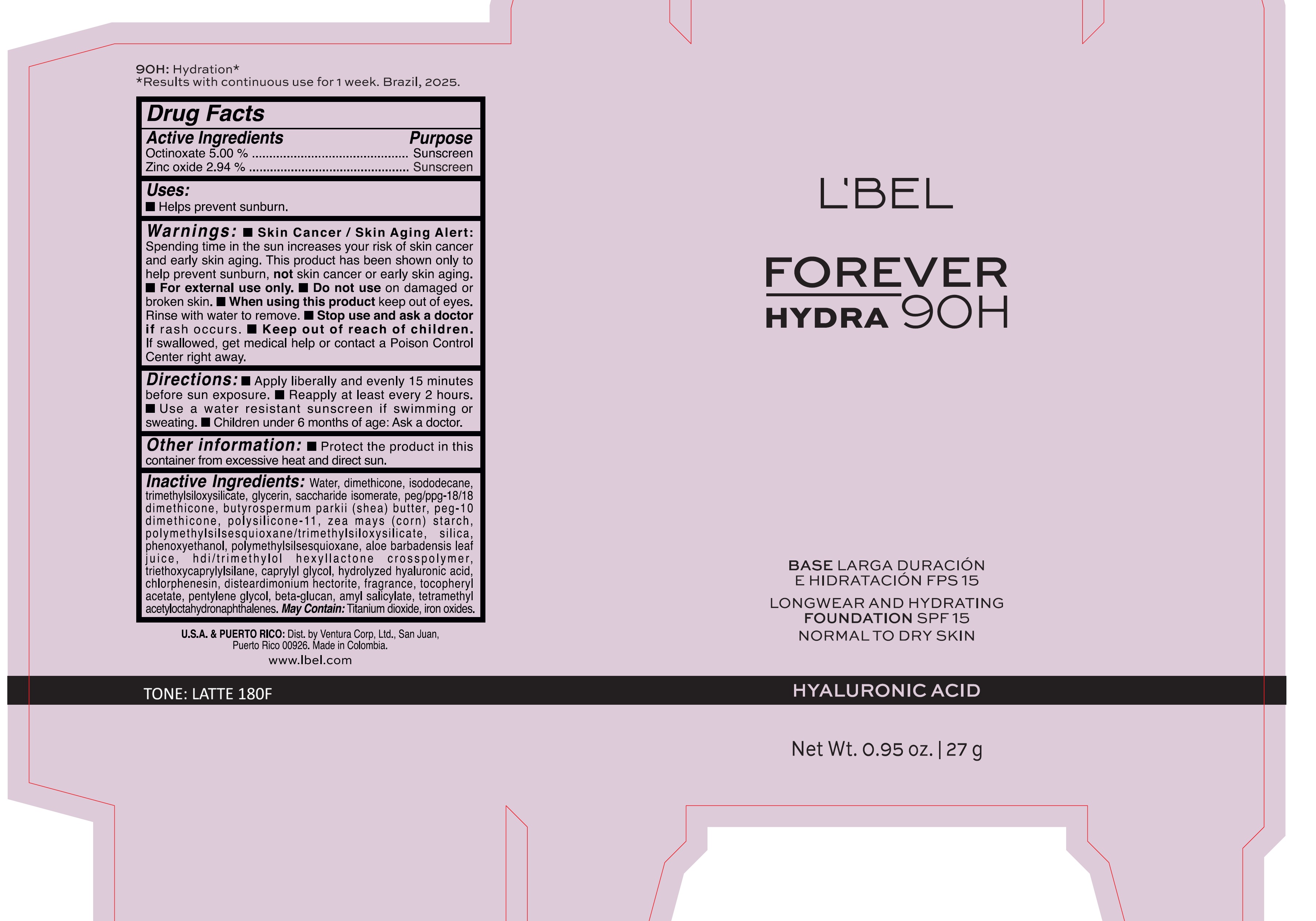 DRUG LABEL: LBEL FOREVER HYDRA LONGWEAR AND HYDRATING FOUNDATION 90H SPF 15 BEIGE 220C
NDC: 14141-388 | Form: EMULSION
Manufacturer: BEL STAR S.A.
Category: otc | Type: HUMAN OTC DRUG LABEL
Date: 20250522

ACTIVE INGREDIENTS: OCTINOXATE 50 mg/1 g; ZINC OXIDE 29.4 mg/1 g
INACTIVE INGREDIENTS: CI 77492; CI 77499; POLYMETHYLSILSESQUIOXANE (4.5 MICRONS); PEG/PPG-18/18 DIMETHICONE; AMYL SALICYLATE; TETRAMETHYL ACETYLOCTAHYDRONAPHTHALENES; ALPHA-TOCOPHEROL ACETATE; TRIETHOXYCAPRYLYLSILANE; CAPRYLYL GLYCOL; PEG-10 DIMETHICONE (220 CST); PHENOXYETHANOL; DISTEARDIMONIUM HECTORITE; GLYCERIN; HDI/TRIMETHYLOL HEXYLLACTONE CROSSPOLYMER; ISODODECANE; SACCHARIDE ISOMERATE; WATER; SHEA BUTTER; ZEA MAYS (CORN) STARCH; TITANIUM DIOXIDE; POLYMETHYLSILSESQUIOXANE/TRIMETHYLSILOXYSILICATE; ALOE VERA LEAF JUICE; DIMETHICONE; CHLORPHENESIN; SILICON DIOXIDE; PENTYLENE GLYCOL; DIMETHICONE/VINYL DIMETHICONE CROSSPOLYMER (SOFT PARTICLE); TRIMETHYLSILOXYSILICATE (M/Q 0.6-0.8); CI 77491

LBEL FOREVER HYDRA LONGWEAR AND HYDRATING FOUNDATION 90H SPF 15

Active Ingredients

OCTINOXATE 5.00 %

ZINC OXIDE 2.94 %

Purpose

Sunscreen

Uses

- Helps prevent sunburn

Warnings

- Skin Cancer / Skin Aging Alert: Spending time in the sun increases your risk of skin cancer and early skin aging. This product has been shown only to help prevent sunburn, not skin cancer or early skin aging.
- For external use only.

Do not use

on damaged or broken skin.

When using this product

keep out of eyes. Rinse with water to remove.

Stop use and ask a doctor if

rash occurs.

Keep out of reach of children.

If swallowed, get medical help or contact a Poison Control Center right away.

Directions

- Apply liberally and evenly 15 minutes before sun exposure
- Reapply at least every 2 hours.
- Use a water resistant sunscreen if swimming or sweating.
- Children under 6 months of age: Ask a doctor.

Other information

- Protect the product in this container from excessive heat and direct sun.

Inactive ingredients

Water, dimethicone, isododecane, trimethylsiloxysilicate, glycerin, saccharide isomerate, peg/ppg-18/18 dimethicone, butyrospermum parkii (shea) butter, peg-10 dimethicone, polysilicone-11, zea mays (corn) starch, polymethylsilsesquioxane/trimethylsiloxysilicate, silica, phenoxyethanol, polymethylsilsesquioxane, aloe barbadensis leaf juice, hdi/trimethylol hexyllactone crosspolymer, triethoxycaprylylsilane, caprylyl glycol, hydrolyzed hyaluronic acid, chlorphenesin, disteardimonium hectorite, fragrance, tocopheryl acetate, pentylene glycol, beta-glucan, amyl salicylate, tetramethyl acetyloctahydronaphthalenes.

May Contain: Titanium dioxide, iron oxides.